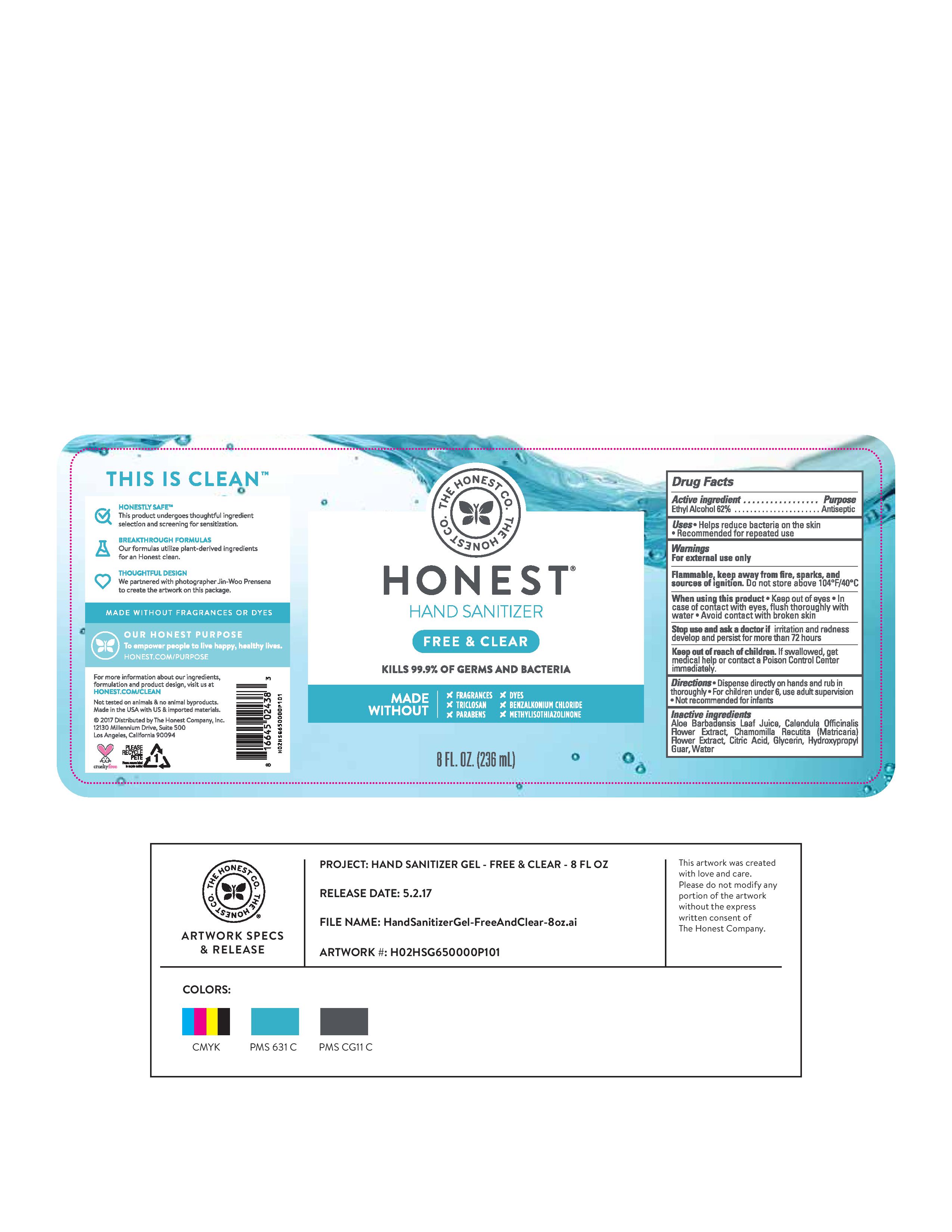 DRUG LABEL: Hand Sanitizer
NDC: 69366-314 | Form: GEL
Manufacturer: The Honest Company
Category: otc | Type: HUMAN OTC DRUG LABEL
Date: 20210125

ACTIVE INGREDIENTS: ALCOHOL 62 mL/100 mL
INACTIVE INGREDIENTS: ALOE VERA LEAF; GLYCERIN; CALENDULA OFFICINALIS FLOWER; CHAMOMILE; GUARAPROLOSE (1300 MPA.S AT 1%); WATER; CITRIC ACID MONOHYDRATE

Honest Hand Sanitizer Gel Free & Clear 8 oz

Active ingredient

Ethyl Alcohol 62%

Purpose

Antisesptic

Uses

Helps reduce bacteria on the skin

Recommended for repeated use

Warnings

For external use only

Flammable, keep away from fire, sparks, and sources of ignition. Do not store above 104 oF/40 oC

When using this product keep out of eyes. In case of contact with eyes, flush thoroughly with water. Avoid contact with broken skin

Stop use and ask a doctor if irritation and redness devleop and persist for more than 72 hours

Keep out of reach of children. If swallowed, get medical help or contact a Poison Control Center immediately.

Directions

Dispense directly on hands and rub in thoroughly

For children under 6, use adult supervision

Not recommended for infants

Inactive ingredients

Aloe Barbadensis Leaf Juice, Calendula Officinalis Flower Extract, Chamomilla Recutita (Matricaria) Flower Extract, Citric Acid, Glycerin, Hydroxypropyl Guar, Water